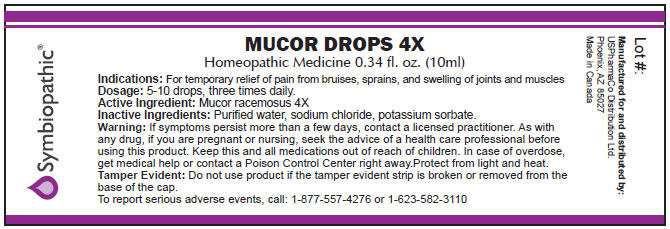 DRUG LABEL: Mucor
NDC: 49693-1301 | Form: LIQUID
Manufacturer: USPharmaCo
Category: homeopathic | Type: HUMAN OTC DRUG LABEL
Date: 20091223

ACTIVE INGREDIENTS: Mucor racemosus 4 [hp_X]/10 mL

MUCOR
DROPS 4X

Homeopathic Medicine

Indications

For temporary relief of pain from bruises, sprains, and swelling of joints and muscles

Dosage

5-10. drops, three times daily.

Active Ingredient

Mucor racemosus 4X

Inactive Ingredients

Purified water, sodium chloride, potassium sorbate.

Warning

If symptoms persist more than a few days, contact a licensed practitioner. As with any drug, if you are pregnant or nursing, seek the advice of a health care professional before using this product.

KEEP OUT OF REACH OF CHILDREN

Keep this and all medications out of reach of children. In case of overdose, get medical help or contact a Poison Control Center right away.

STORAGE AND HANDLING

Protect from light and heat.

Tamper Evident

Do not use product if the tamper evident strip is broken or removed from the base of the cap.

To report serious adverse events, call: 1-877-557-4276 or 1-623-582-3110

Manufactured for and distributed by:
USPharmaCo Distribution Ltd.
2205 W. Lone Cactus Drive #19,
Phoenix, AZ 85027
www.uspharmaco.com
info@uspharmaco.com

Made in Canada

PRINCIPAL DISPLAY PANEL - 10 ml Label

MUCOR DROPS 4X

Homeopathic Medicine 0.34 fl. oz. (10ml)

Indications: For temporary relief of pain from bruises, sprains, and swelling of joints and muscles
Dosage: 5-10 drops, three times daily.
Active Ingredient: Mucor racemosus 4X
Inactive Ingredients: Purified water, sodium chloride, potassium sorbate.
Warning: If symptoms persist more than a few days, contact a licensed practitioner. As with
any drug, if you are pregnant or nursing, seek the advice of a health care professional before
using this product. Keep this and all medications out of reach of children. In case of overdose,
get medical help or contact a Poison Control Center right away.Protect from light and heat.
Tamper Evident: Do not use product if the tamper evident strip is broken or removed from the
base of the cap.
To report serious adverse events, call: 1-877-557-4276 or 1-623-582-3110